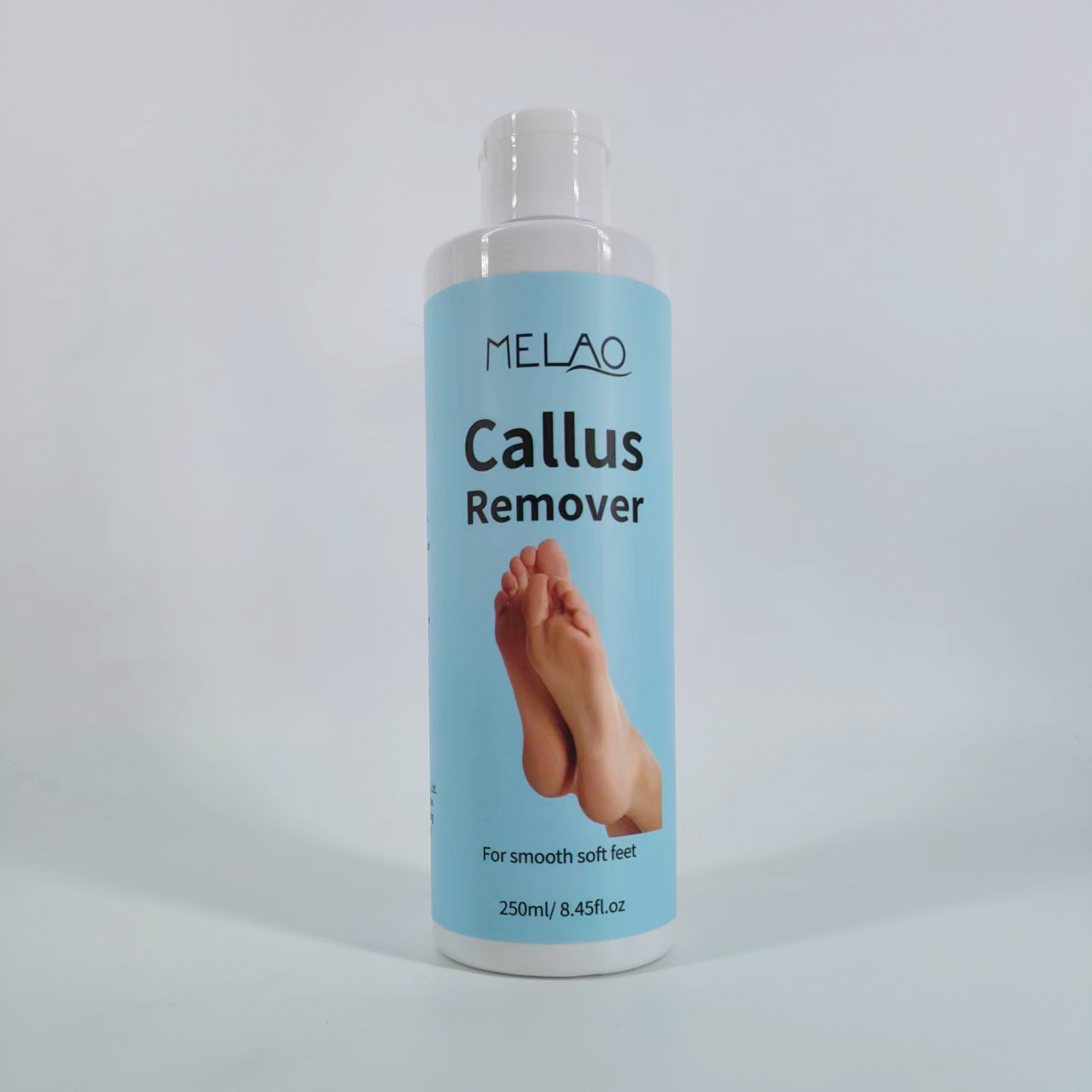 DRUG LABEL: MELAO Callus Remover
NDC: 74458-276 | Form: GEL
Manufacturer: Guangzhou Yilong Cosmetics Co., Ltd
Category: otc | Type: HUMAN OTC DRUG LABEL
Date: 20241028

ACTIVE INGREDIENTS: PUMICE 5 g/100 mL; UREA 10 g/100 mL
INACTIVE INGREDIENTS: POTASSIUM HYDROXIDE; MENTHYL LACTATE; LAURYL LAURATE; GLYCERIN; METHYL DIISOPROPYL PROPIONAMIDE; ZEA MAYS (CORN) STARCH; CARBOMER HOMOPOLYMER, UNSPECIFIED TYPE; ETHYL MENTHANE CARBOXAMIDE; WATER

MELAO Callus Remover

ACTIVE INGREDIENT

Pumice Extract

Urea

INACTIVE INGREDIENT

Water

Potassium Hydroxide

Glycerin

Carbomer

Methyl Diisopropyl Propionamide

Ethyl Menthane Carboxamide

Menthyl Lactate

Lauryl Laurate

Zea Mays (Corn) Starch

INDICATIONS AND USAGE

Put Gloves on.
1. Soak feet in warm water until prune-like.

2. Pre scrub with pumice stone or foot rasp.(Optional but recommended)
3. Towel dry one foot, apply callus remover to hard and dry callused areas(avoid soft skin), and let sit for 5-10 minutes.

4. You can scrub with pumice or rasp while callus remover is on.(Optional but recommended)
5. Rinse foot and use pumice stone or rasp to remove extra residue of callus remover and dead skin.
6.Repeat above process for other foot.

Note: Some peoples calluses maybe worse than others,so repeat callus remover process as necessary.

PURPOSE

Exfoliate your feet.

WARNINGS

For external use only.

Stop use and ask a doctor if rash occurs.

Do not use on damaged or broken skin.

When using this product keep out of eyes. Rinse with water to remove.

Keep out of reach of children. If swallowed, get medical help or contact a Poison Control Center right away.

DOSAGE AND ADMINISTRATION

Put Gloves on.
1. Soak feet in warm water until prune-like.

2. Pre scrub with pumice stone or foot rasp.(Optional but recommended)
3. Towel dry one foot, apply callus remover to hard and dry callused areas(avoid soft skin), and let sit for 5-10 minutes.

4. You can scrub with pumice or rasp while callus remover is on.(Optional but recommended)
5. Rinse foot and use pumice stone or rasp to remove extra residue of callus remover and dead skin.
6.Repeat above process for other foot.

Note: Some peoples calluses maybe worse than others,so repeat callus remover process as necessary.